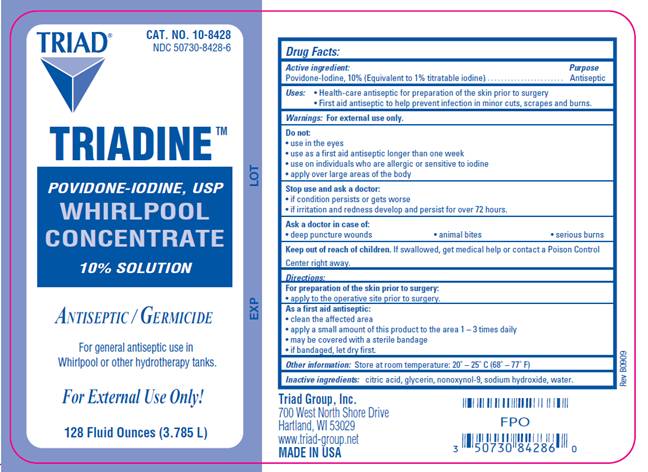 DRUG LABEL: Triadine Whirlpool
NDC: 50730-8428 | Form: SOLUTION
Manufacturer: H and P Industries, Inc. dba Triad Group
Category: otc | Type: HUMAN OTC DRUG LABEL
Date: 20091214

ACTIVE INGREDIENTS: povidone-iodine .10 L/1 L
INACTIVE INGREDIENTS: citric acid monohydrate; glycerin; sodium hydroxide; water

DRUG FACTS

ACTIVE INGREDIENT

Povidone Iodine,10% (Equivalent to 1% titratable iodine)

PURPOSE

Antiseptic

USES

- Health-care antiseptic for preparation of the skin prior to surgery
- First id antiseptic to help prevent the risk of infection in minor cuts, scrapes and burns.

WARNINGS

For external use only.

Do not use

- in the eyes
- use as a first aid antiseptic for longer than one week
- use on individuals who are allergic or sensitive to iodine
- apply over large areas of the body

Ask a doctor in case of

- deep or puncture wounds
- animal bites
- serious burns

Stop use and ask a doctor

- if condition persists or gets worse
- if irritation and redness develop and persist for over 72 hours.

Keep out of reach of children

If swallowed, get medical help or contact a Poison Control Center right away.

DIRECTIONS

For preparation of the skin prior to surgery:

- apply to the operative site prior to surgery

As a first aid antiseptic

- clean the affected area
- apply a small amount of this product to the area 1-3 times daily
- may be covered with a sterile bandage
- if bandaged, let dry first

OTHER INFORMATION

Store at room temperature 20° - 25° C (68° - 77° F)

INACTIVE INGREDIENTS

citric acid, glycerin, nonoxynol-9, sodium hydroxide, water

LABEL INFORMATION

Triad
Cat. No. 10-8428
NDC 50730-8428-6
TRIADINE
POVIDONE-IODINE, USP
WHIRLPOOL CONCENTRATE
10% Solution
Antiseptic / Germicide

For general antiseptic use in Whirlpool or other hydrotherapy tanks.
For External Use Only!
128 Fluid Ounces (3.785 L)